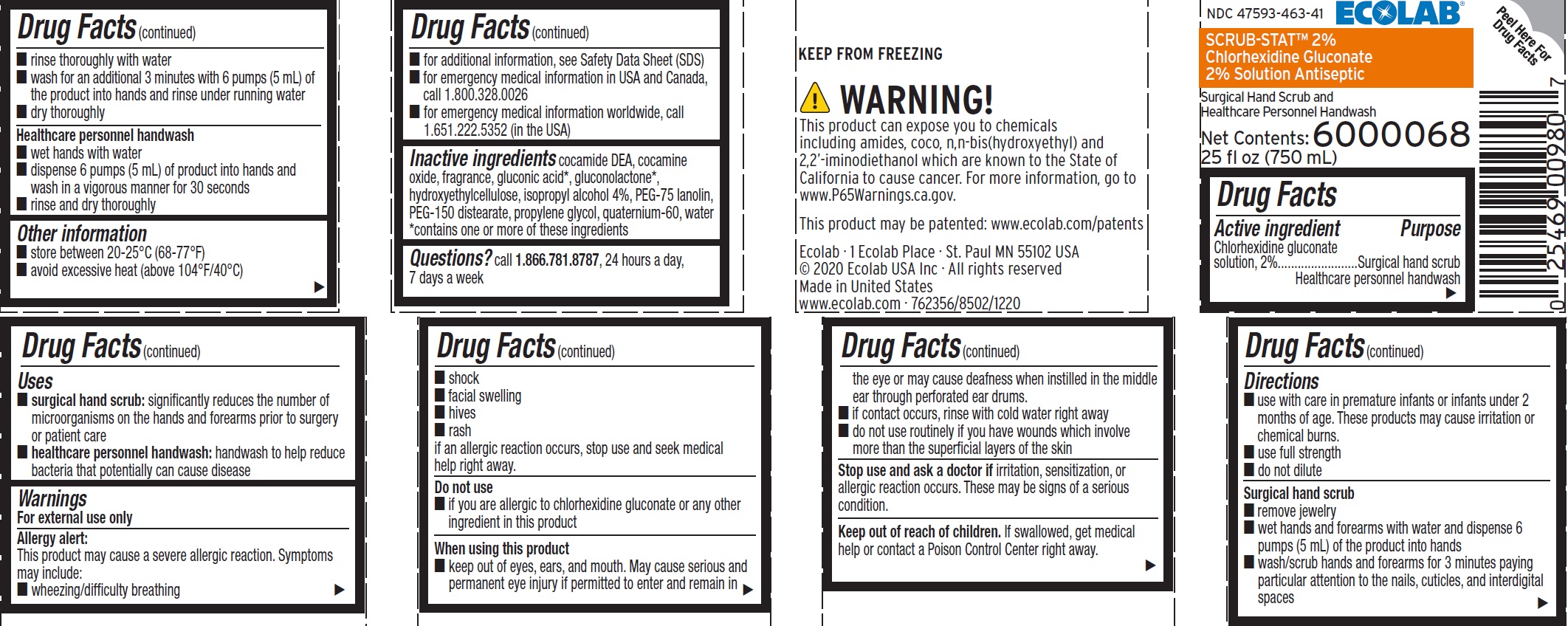 DRUG LABEL: Scrub-Stat
NDC: 47593-463 | Form: SOLUTION
Manufacturer: Ecolab Inc.
Category: otc | Type: HUMAN OTC DRUG LABEL
Date: 20260102

ACTIVE INGREDIENTS: CHLORHEXIDINE GLUCONATE 20 mg/1 mL
INACTIVE INGREDIENTS: COCO DIETHANOLAMIDE; COCAMINE OXIDE; GLUCONIC ACID; GLUCONOLACTONE; HYDROXYETHYL CELLULOSE (3000 CPS AT 1%); ISOPROPYL ALCOHOL; PEG-75 LANOLIN; PEG-150 DISTEARATE; PROPYLENE GLYCOL; QUATERNIUM-33; WATER

Drug Facts

Active ingredient

Chlorhexidine gluconate solution, 2%

Purpose

Surgical hand scrub

Healthcare personnel handwash

Uses

- surgical hand scrub: significantly reduces the number of microorganisms on the hands and forearms prior to surgery or patient care
- healthcare personnel handwash: handwash to help reduce bacteria that potentially can cause disease

Warnings

For external use only

Allergy alert:

This product may cause a severe allergic reaction.

Symptoms may include:

- wheezing/difficulty breathing
- shock
- facial swelling
- hives
- rash

if an allergic reaction occurs, stop use and seek medical help right away.

Do not use

- if you are allergic to chlorhexidine gluconate or any other ingredients in this product

When using this product

- keep out of eyes, ears, and mouth. May cause serious and permanent eye injury if permitted to enter and remain in the eye or may cause deafness when instilled in the middle ear through perforated ear drums.
- if contact occurs, rinse with cold water right away
- do not use routinely if you have wounds which involve more than the superficial layers of the skin

Stop use and ask a doctor if

irritation, sensitization, or allergic reaction occurs. These may be signs of a serious condition.

Keep out of reach of children. If swallowed, get medical help or contact a Poison Control Center right away.

Directions

- use with care in premature infants or infants under 2 months of age. These products may cause irritation or chemical burns.
- use full strength
- do not dilute

Surgical hand scrub

- remove jewelry
- wet hands and forearms with water and dispense 6 pumps (5 mL) of the product onto hands
- wash/scrub hands and forearms for 3 minutes paying particular attention to the nails, cuticles, and interdigital spaces
- rinse thoroughly with water
- wash for an additional 3 minutes with 6 pumps (5 mL) of the product into hands and rinse under running water
- dry thoroughly

Healthcare personnel handwash

- wet hands with water
- dispense 6 pumps (5 mL) of product into hands and wash in a vigorous manner for 30 seconds
- rinse and dry thoroughly

Other information

- store between 20-25°C (68-77°F)
- avoid excessive heat (above 104°F/40°C)
- for additional information, see Safety Data Sheet (SDS)
- for emergency medical information in USA and Canada, call 1.800.328.0026
- for emergency medical information worldwide, call 1.651.222.5352 (in the USA)

INACTIVE INGREDIENT

Inactive ingredients cocamide DEA, cocamine oxide, fragrance, gluconic acid*, gluconolactone*, hydroxyehtylcellulose, isopropyl alcohol 4%, PEG-75 lanolin, PEG-150 distearate, propylene glycol, quaternium-60, water

*contains one or more of these ingredients

QUESTIONS

Questions? call 1.866.781.8787, 24 hours a day, 7 days a week.

Representative label and principal display panel

ECOLAB®

NDC 47596-463-41

SCRUB-STAT 2%

Chorhexidine Gluconate 2% Solution Antiseptic

Surgical Hand Scrub and

Healthcare Personnel Handwash

6000068

Net Content:

25 fl oz (750 mL)

KEEP FROM FREEZING

Ecolab • 1 Ecolab Place • St Paul MN 55102 USA

© 2020 Ecolab USA Inc • All rights reserved

Made in United States

www.ecolab.com • 762356/8502/1220